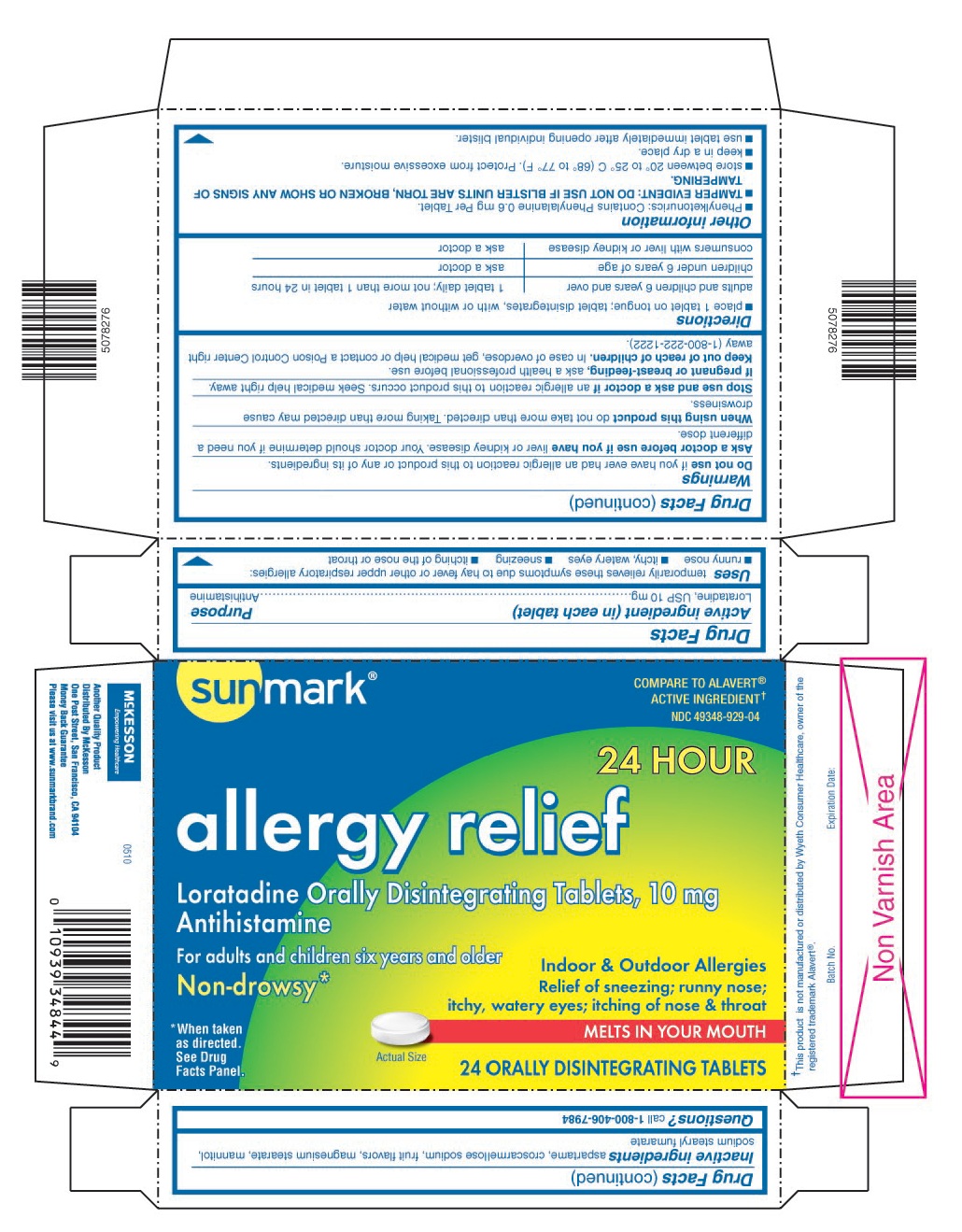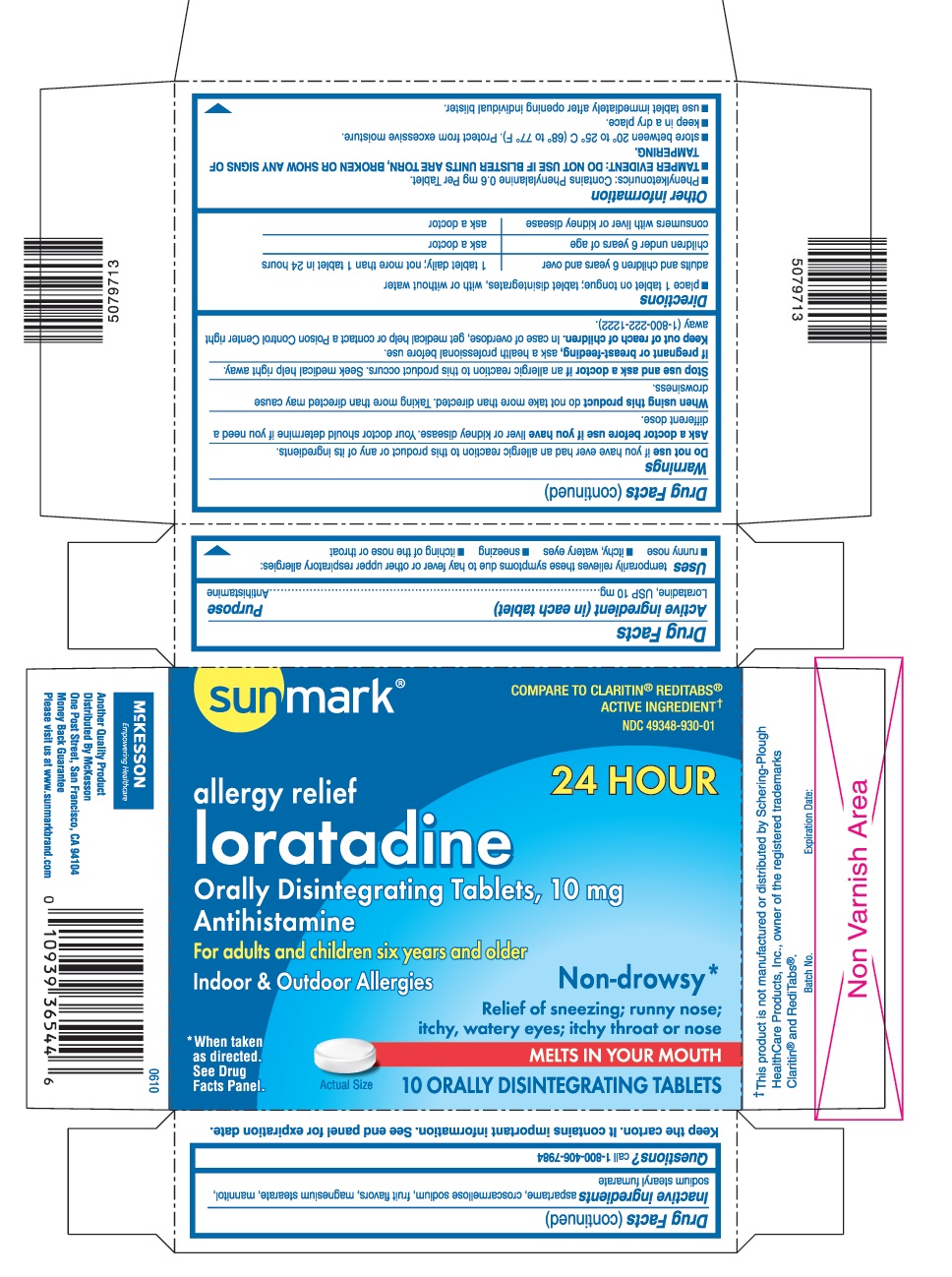 DRUG LABEL: Sunmark Loratadine ODT
NDC: 49348-930 | Form: TABLET, ORALLY DISINTEGRATING
Manufacturer: Sunmark
Category: otc | Type: HUMAN OTC DRUG LABEL
Date: 20120814

ACTIVE INGREDIENTS: LORATADINE 10 mg/1 1
INACTIVE INGREDIENTS: ASPARTAME; CROSCARMELLOSE SODIUM; MAGNESIUM STEARATE; MANNITOL; SODIUM STEARYL FUMARATE

Drug Facts

ACTIVE INGREDIENT (IN EACH TABLET)

Loratadine, USP 10 mg

PURPOSE

Antihistamine

USES

temporarily relieves these symptoms due to hay fever or other upper respiratory allergies:

- runny nose
- itchy, watery eyes
- sneezing
- itching of the nose or throat

WARNINGS

Do not use

if you have ever had an allergic reaction to this product or any of its ingredients.

Ask a doctor before use if you have

liver or kidney disease. Your doctor should determine if you need a different dose.

When using this product

do not take more than directed. Taking more than directed may cause drowsiness.

Stop use and ask a doctor if

an allergic reaction to this product occurs. Seek medical help right away.

If pregnant or breast-feeding,

ask a health professional before use.

Keep out of reach of children.

In case of overdose, get medical help or contact a Poison Control Center right away (1-800-222-1222).

DIRECTIONS

- place 1 tablet on tongue; tablet disintegrates, with or without water
  adults and children 6 years and over | 1 tablet daily; not more than 1 tablet in 24 hours
  children under 6 years of age | ask a doctor
  consumers with liver or kidney disease | ask a doctor

OTHER INFORMATION

- Phenylketonurics: Contains Phenylalanine 0.6 mg Per Tablet.
- TAMPER EVIDENT: DO NOT USE IF BLISTER UNITS ARE TORN, BROKEN OR SHOW ANY SIGNS OF TAMPERING.
- store between 20° to 25° C (68° to 77° F). Protect from excessive moisture.
- keep in a dry place.
- use tablet immediately after opening individual blister.

INACTIVE INGREDIENTS

aspartame, croscarmellose sodium, fruit flavors, magnesium stearate, mannitol, sodium stearyl fumarate

QUESTIONS?

call 1-800-406-7984

Keep the carton. It contains important information.

See end panel for expiration date.

Distributed by McKesson

One Post Street, San Francisco, CA 94104

www.sunmarkbrand.com

PRINCIPAL DISPLAY PANEL

sunmark®

NDC 49348-930-01

allergy relief

24 HOUR

loratadine Orally Disintegrating Tablets, 10 mg

Antihistamine

For adults and children six years and older

Indoor & Outdoor Allergies

Non-drowsy*

Relief of sneezing; runny nose; itchy, watery eyes; itchy throat or nose

MELTS IN YOUR MOUTH

10 ORALLY DISINTEGRATING TABLETS

* When taken as directed.

See Drug Facts Panel.

COMPARE TO CLARITIN® REDITABS® ACTIVE INGREDIENT†

† The product is not manufactured or distributed by Schering-Plough Healthcare Products , Inc.

CLARITIN® and REDITABS® are registered trademarks of Schering Corporation.

sunmark®

NDC 49348-929-04

allergy relief

24 HOUR

Loratadine Orally Disintegrating Tablets, 10 mg

Antihistamine

For adults and children six years and older

Indoor & Outdoor Allergies

Non-drowsy*

Relief of sneezing; runny nose; itchy, watery eyes; itching of nose & throat

MELTS IN YOUR MOUTH

24 ORALLY DISINTEGRATING TABLETS

* When taken as directed.

See Drug Facts Panel.

COMPARE TO ALAVERT® ACTIVE INGREDIENT†

† The product is not manufactured or distributed by Wyeth Consumer Healthcare, owner of the registered trademark Alavert®.